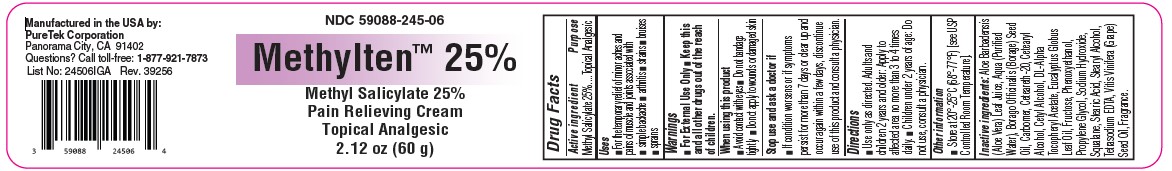 DRUG LABEL: Methylten 25%
NDC: 59088-245 | Form: CREAM
Manufacturer: PureTek Corporation
Category: otc | Type: HUMAN OTC DRUG LABEL
Date: 20250612

ACTIVE INGREDIENTS: METHYL SALICYLATE 250 mg/1 g
INACTIVE INGREDIENTS: PHENOXYETHANOL; EUCALYPTUS OIL; WATER; ALOE VERA LEAF; STEARYL ALCOHOL; .ALPHA.-TOCOPHEROL ACETATE; SODIUM HYDROXIDE; SQUALANE; BORAGE SEED OIL; CETYL ALCOHOL; STEARIC ACID; CARBOMER HOMOPOLYMER, UNSPECIFIED TYPE; CETOSTEARYL ALCOHOL; FRUCTOSE; POLYOXYL 20 CETOSTEARYL ETHER; PROPYLENE GLYCOL; EDETATE SODIUM; GRAPE SEED OIL

NDC 59088-245 Methylten 25%

Active Ingredients

Methyl salicylate 25%

Purpose

Topical analgesic

Uses

■ For the temporary relief of minor aches and pains of muscle and joints associated with ■ simple backache ■ arthritis ■ strains ■ bruises ■ sprains

Warnings

For external use only

KEEP OUT OF REACH OF CHILDREN

Keep this and all other drugs out of the reach of children.

When using this product

■ Avoid contact with eyes ■ Do not bandage tightly ■ Do not apply to wounds or damaged skin

Stop use and ask a doctor if

■ If condition worsens or if symptoms persist for more than 7 days or clear up and occur again within a few days, discontinue use of this product and consult a physician.

Directions

■ Use only as directed. Adults and children 2 years and older: Apply to affected area no more than 3 to 4 times daily. ■ Children under 2 years of age: Do not use, consult a physician.

Other information

■ Store at 20°-25°C (68°-77°F) [see USP Controlled Room Temperature].

Inactive Ingredients

Aloe Barbadensis (Aloe Vera) Leaf Juice, Aqua (Purified Water), Borago Officinalis (Borage) Seed Oil, Carbomer, Ceteareth-20, Cetearyl Alcohol, Cetyl Alcohol, DL-Alpha Tocopheryl Acetate, Eucalyptus Globus Leaf Oil, Fructose, Phenoxyethanol, Propylene Glycol, Sodium Hydroxide, Squalane, Stearic Acid, Stearyl Alcohol, Tetrasodium EDTA, Vitis Vinifera (Grape) Seed Oil, Fragrance.

Methylten™ 25%

Manufactured in the USA by:
PureTek Corporation
Panorama City, CA 91402
Questions? Call toll-free: 1 -877-921-7873